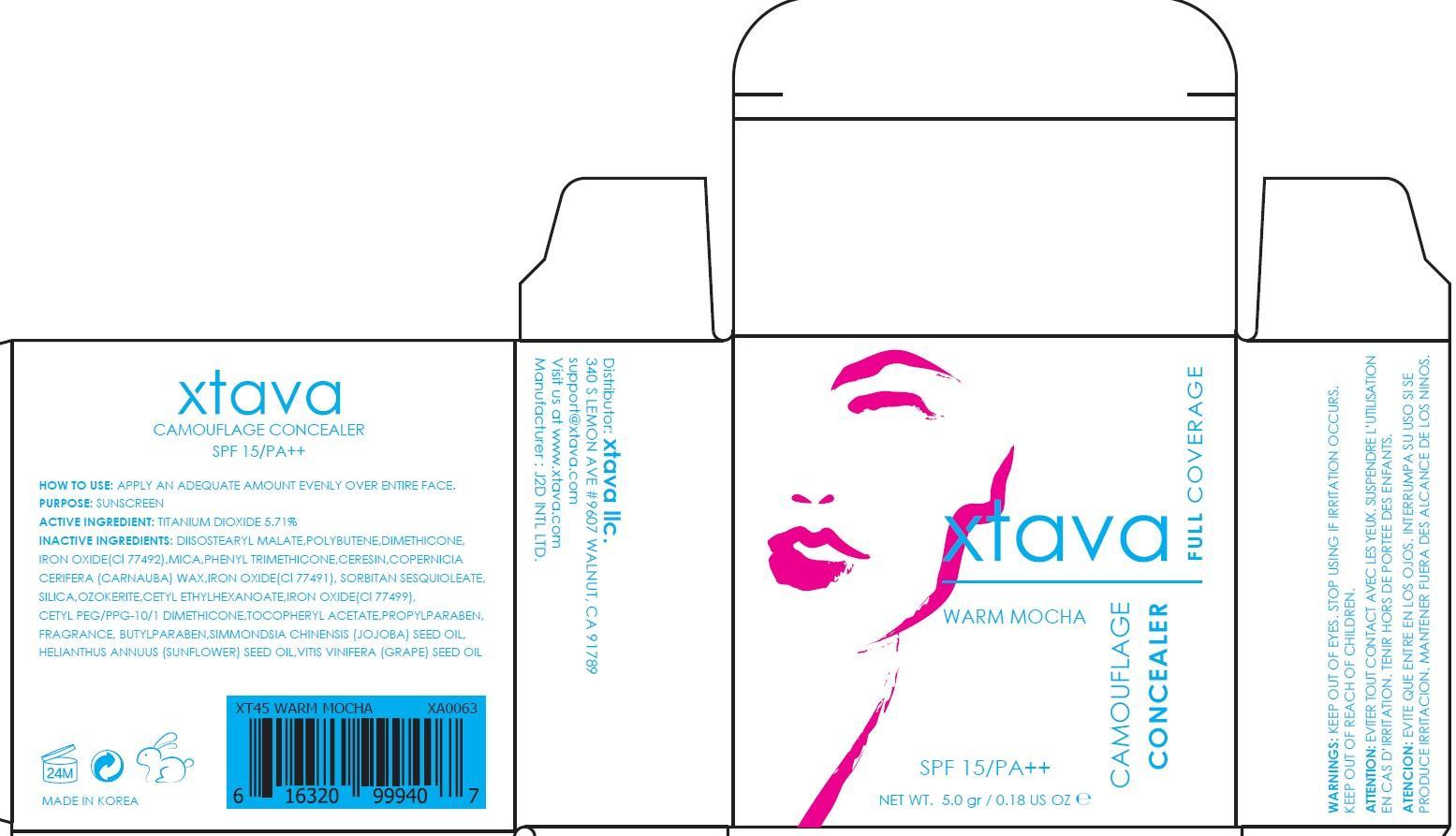 DRUG LABEL: CAMOUFLAGE CONCEALER WARM MOCHA
NDC: 69958-090 | Form: POWDER
Manufacturer: J2D INTERNATIONAL
Category: otc | Type: HUMAN OTC DRUG LABEL
Date: 20150716

ACTIVE INGREDIENTS: Titanium Dioxide 0.28 g/5 g
INACTIVE INGREDIENTS: DIISOSTEARYL MALATE; DIMETHICONE

ACTIVE INGREDIENT

Active Ingredient: Titanium Dioxide 5.71%

INACTIVE INGREDIENT

Inactive Ingredients: DIISOSTEARYL MALATE, POLYBUTENE, DIMETHICONE, IRON OXIDE(Cl 77492), MICA, PHENYL TRIMETHICONE, CERESIN, COPERNICIA CERIFERA (CARNAUBA) WAX, IRON OXIDE(Cl 77491), SORBITAN SESQUIOLEATE, SILICA, OZOKERITE, CETYL ETHYLHEXANOATE, IRON OXIDE(Cl 77499), CETYL PEG/PPG-10/1 DIMETHICONE, TOCOPHERYL ACETATE, PROPYLPARABEN, PERFUME, BUTYLPARABEN, SIMMONDSIA CHINENSIS (JOJOBA) SEED OIL, HELIANTHUS ANNUUS (SUNFLOWER) SEED OIL, VITIS VINIFERA (GRAPE) SEED OIL

PURPOSE

Purpose: Sunscreen

WARNINGS

Warnings: KEEP OUT OF EYES. STOP USING IF IRRITATION OCCURS. KEEP OUT OF REACH OF CHILDREN.

DESCRIPTION

ATTENTION: EVITER TOUT CONTACT AVEC LES YEUX. SUSPENDRE L’UTILISATION EN CAS D’IRRITATION. TENIR HORS DE PORTEE DES ENFANTS.

ATENCION: EVITE QUE ENTRE EN LOS OJOS. INTERRUMPA SU USO SI SE PRODUCE IRRITACION. MANTENER FUERA DES ALCANCE DE LOS NINOS.

How to use: APPLY AN ADEQUATE AMOUNT EVENLY OVER ENTIRE FACE.